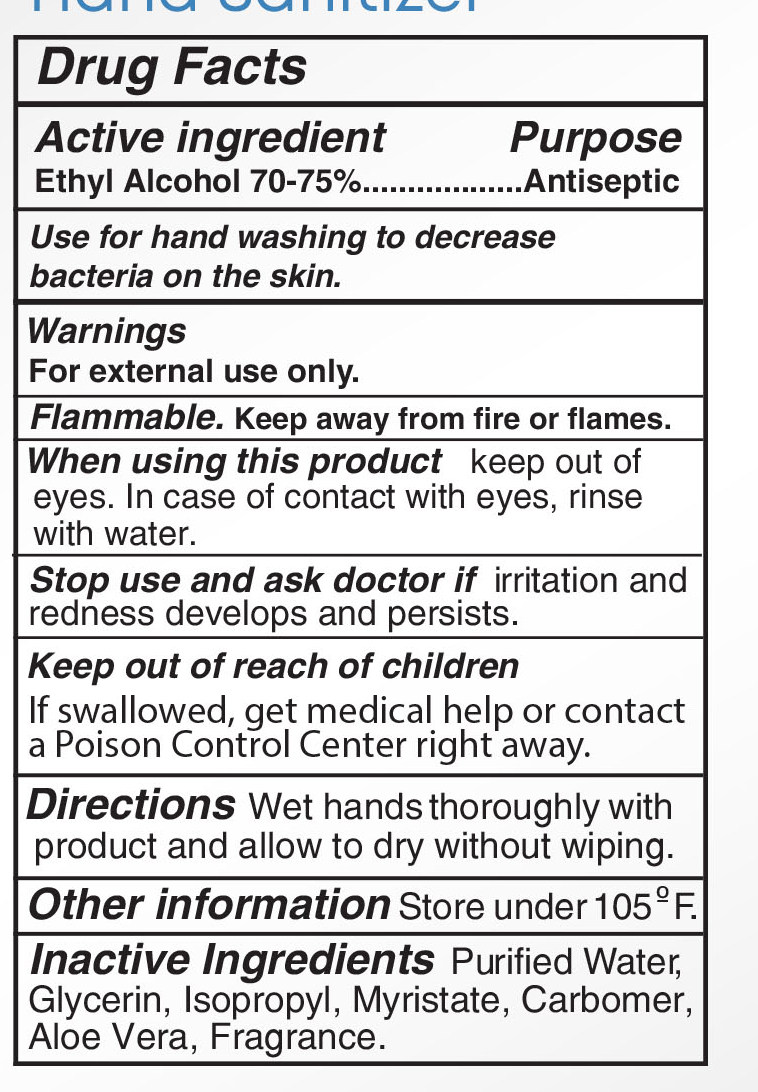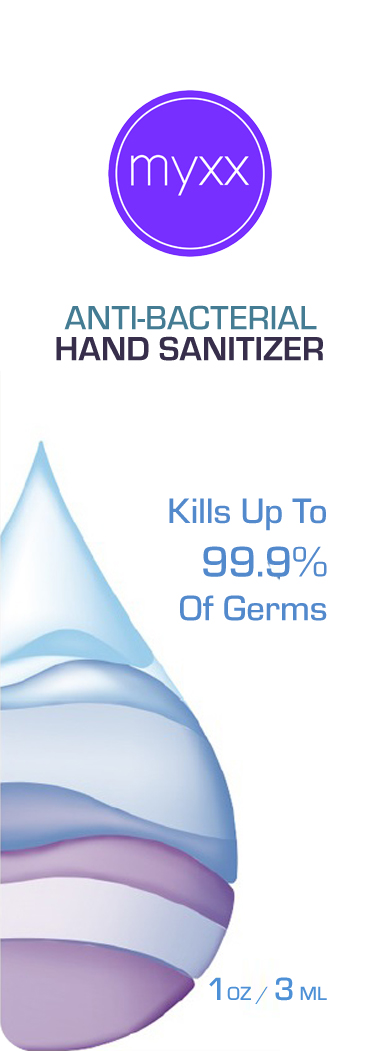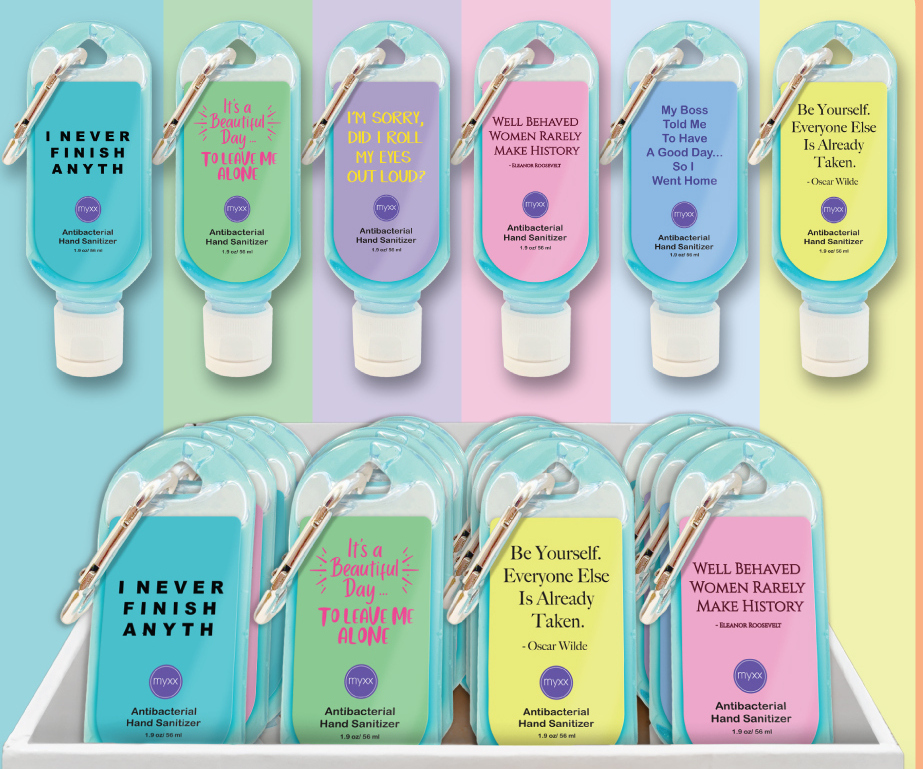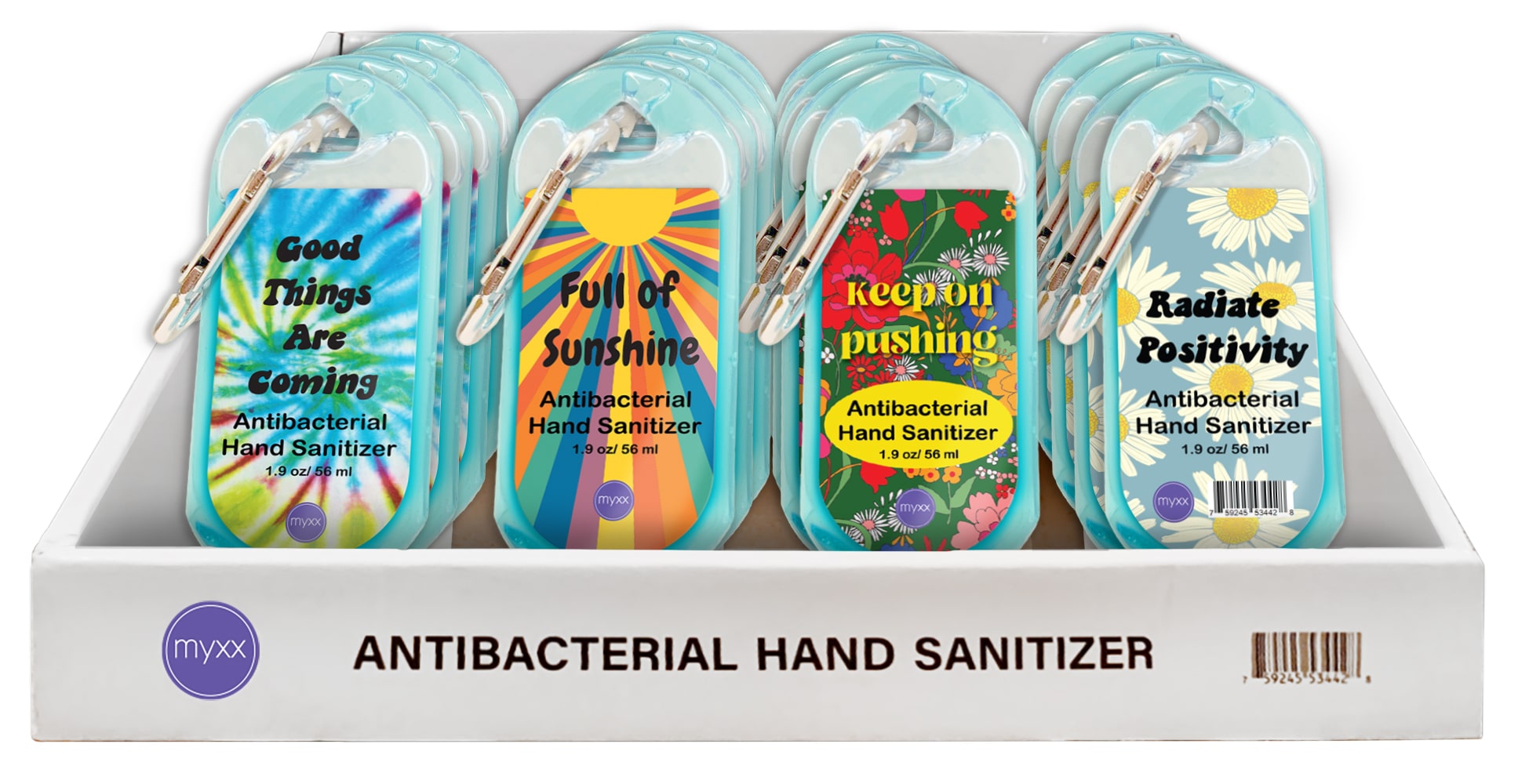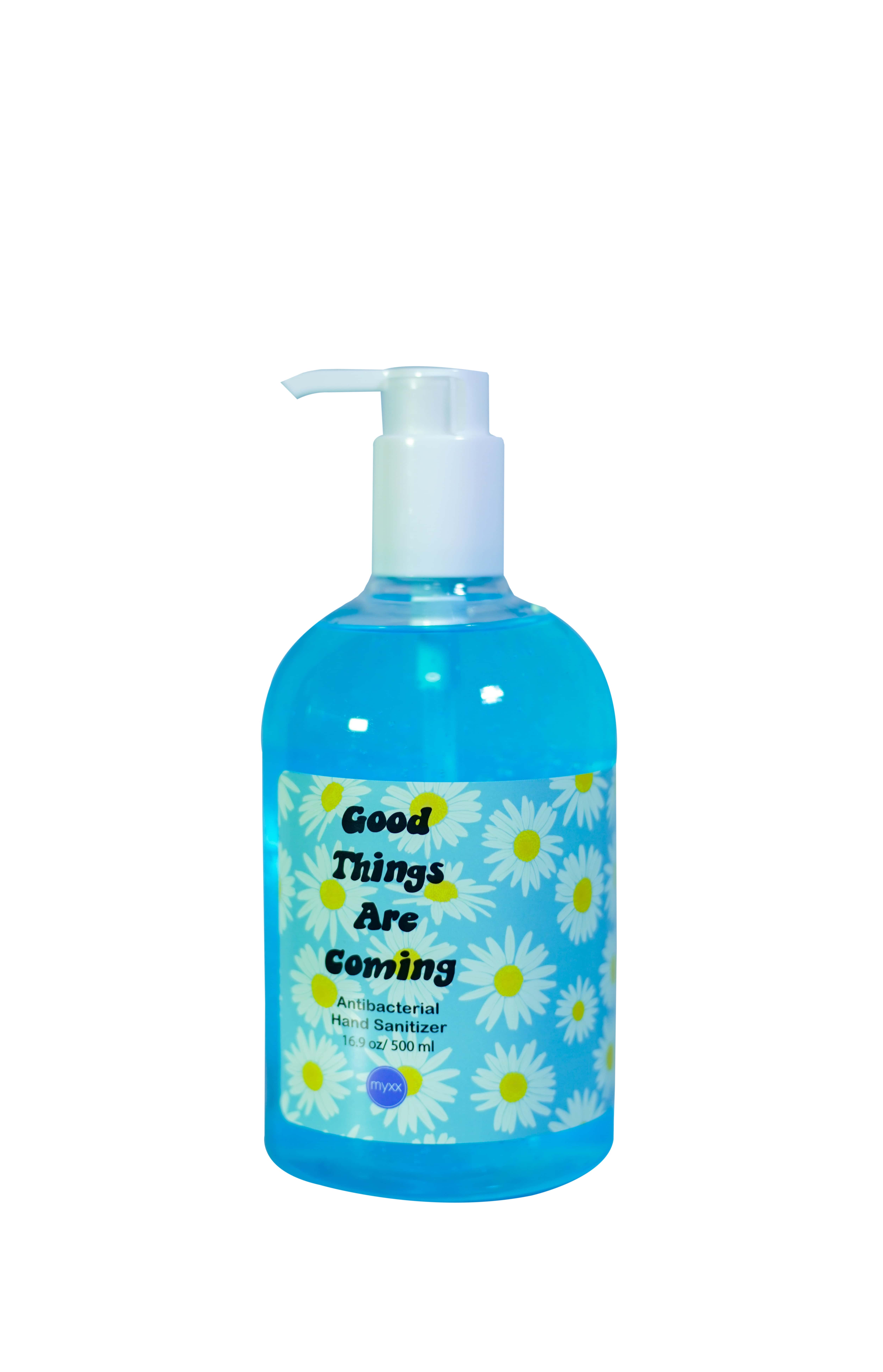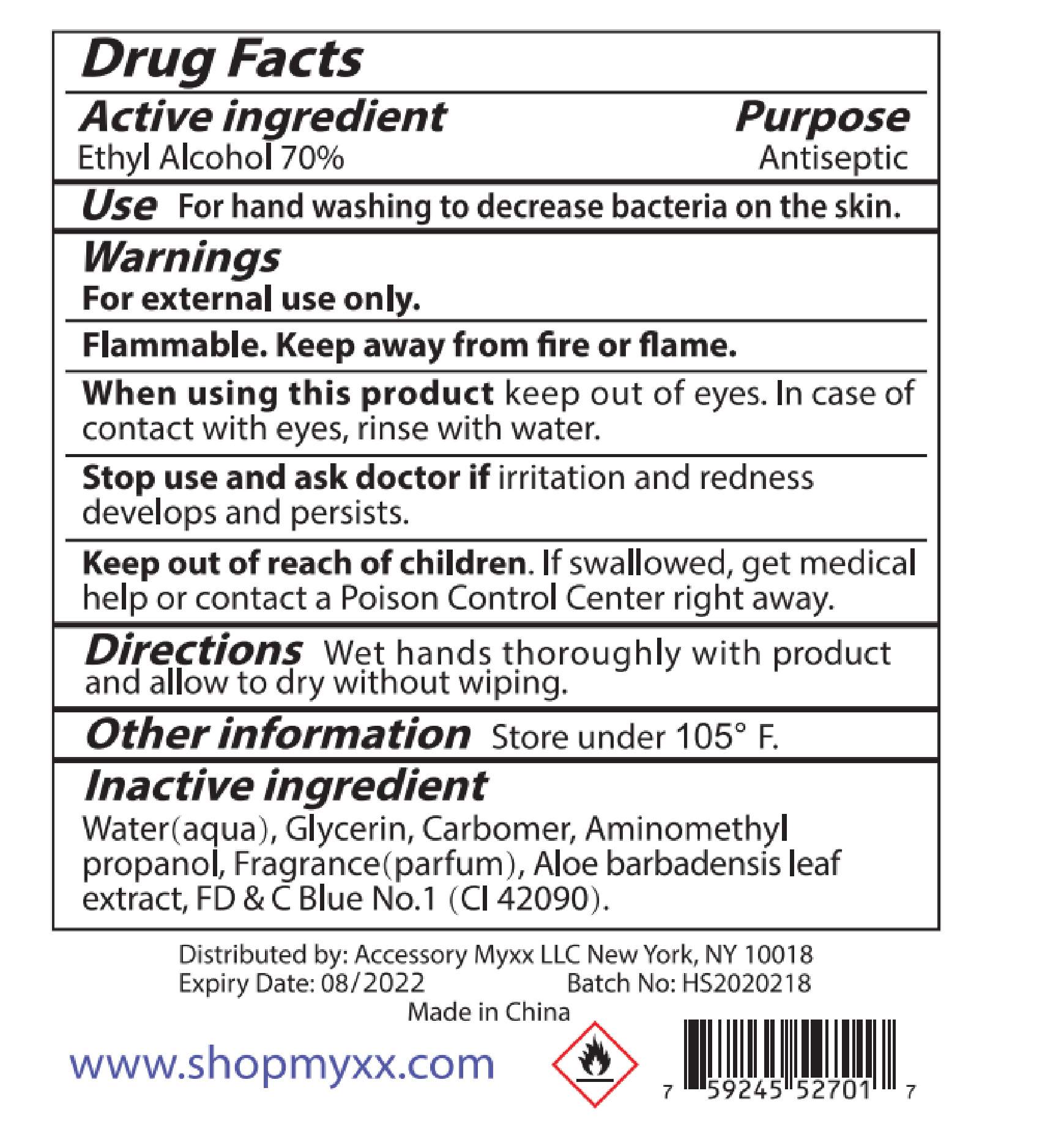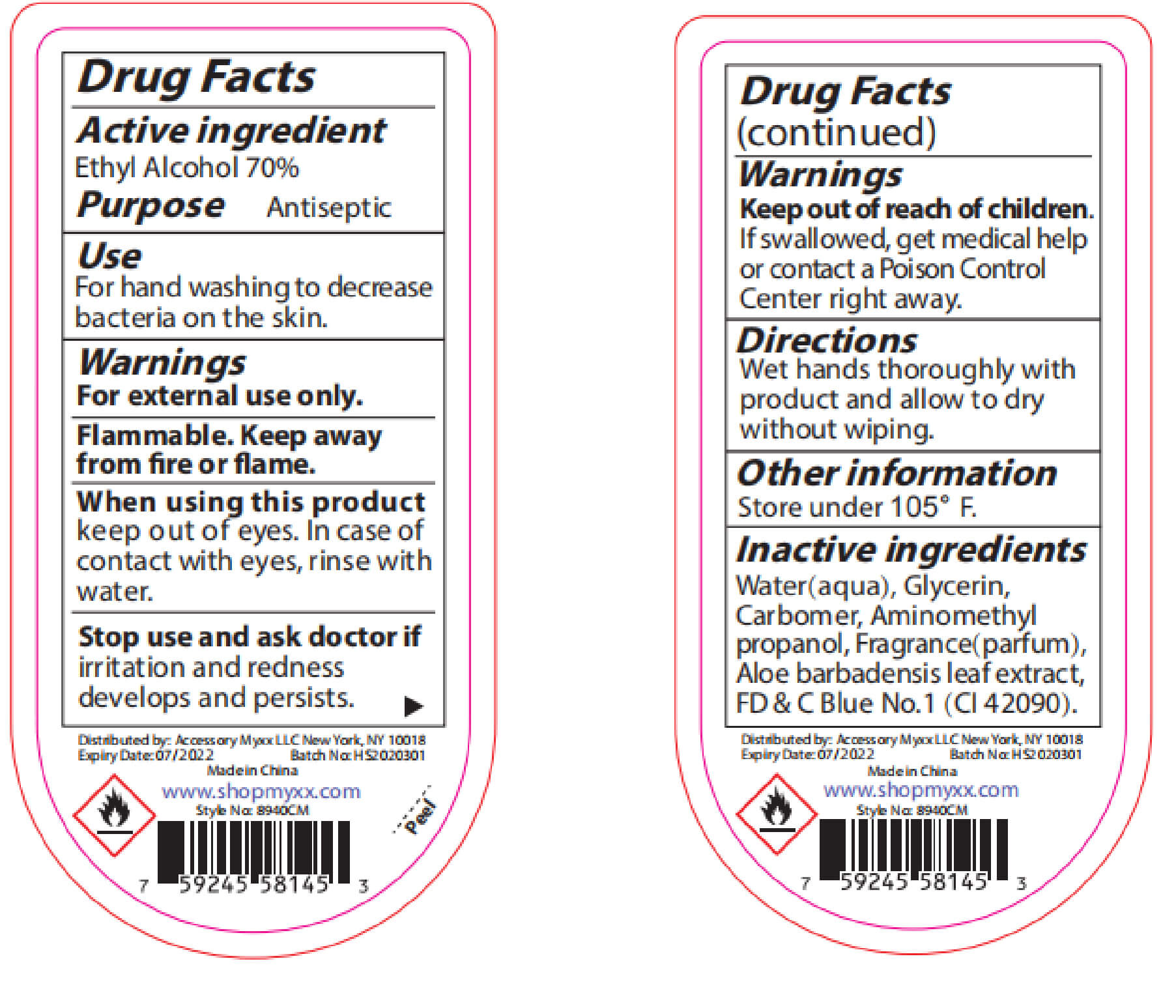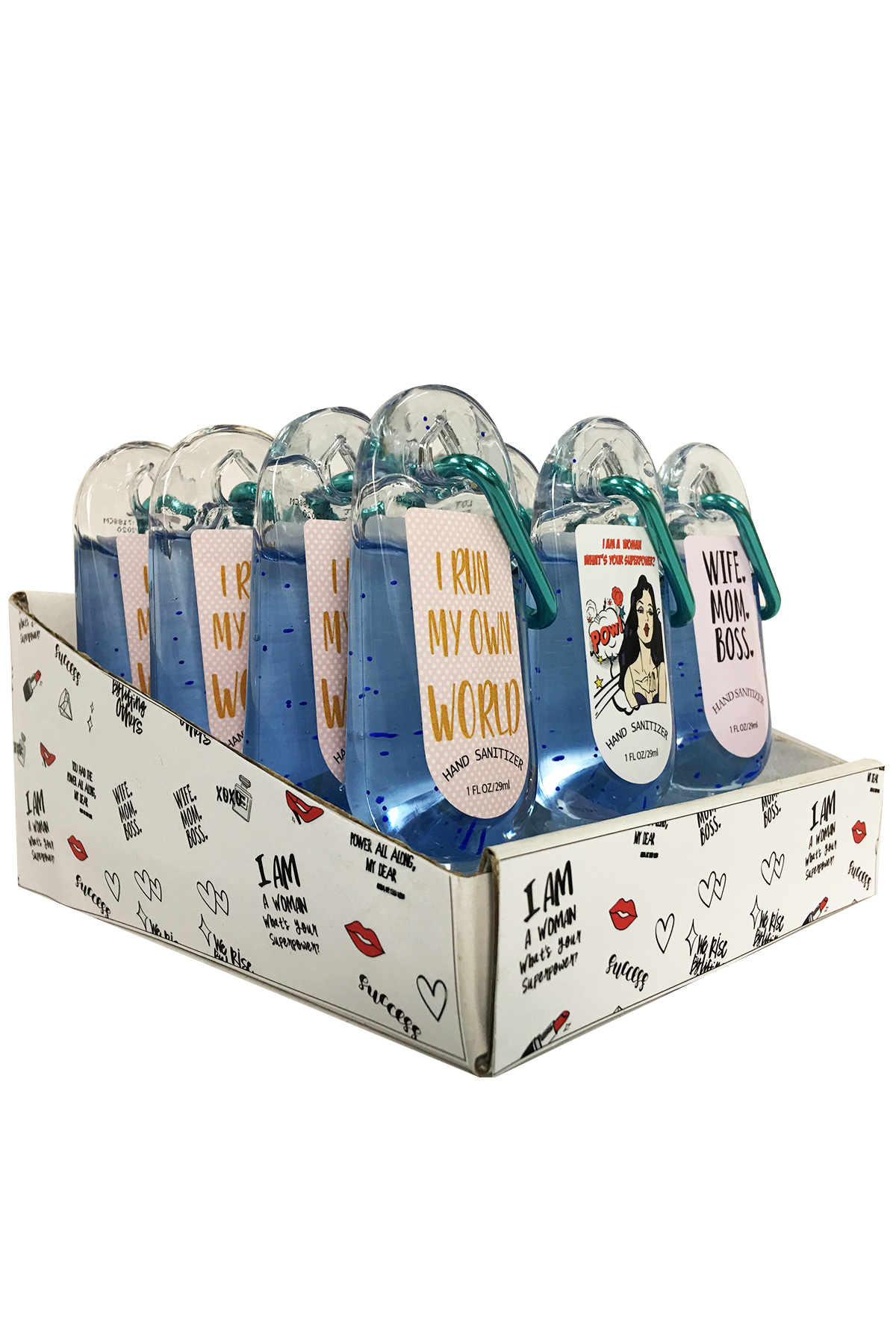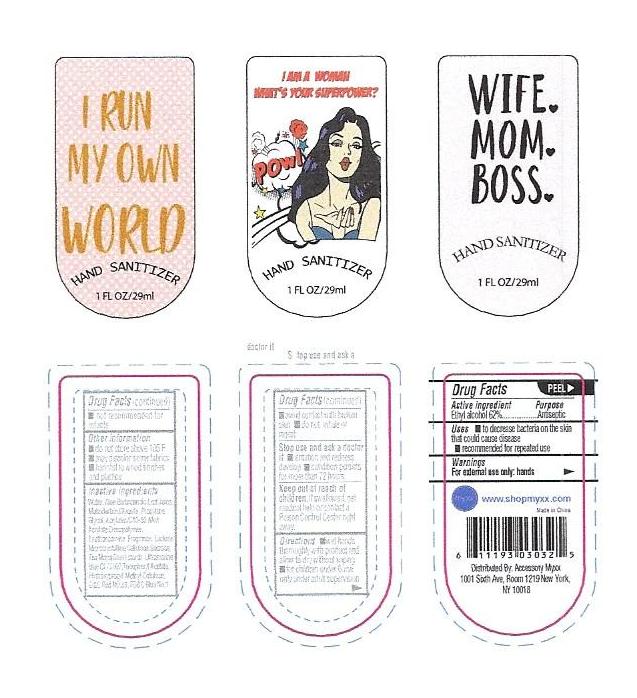 DRUG LABEL: Instant Hand Sanitizer
NDC: 72619-2020 | Form: GEL
Manufacturer: Acessory Myxx LLC
Category: otc | Type: HUMAN OTC DRUG LABEL
Date: 20200519

ACTIVE INGREDIENTS: ALCOHOL 75 mL/100 mL
INACTIVE INGREDIENTS: AMINOMETHYL PROPANEDIOL 0.18 mL/100 mL; WATER 28.42 mL/100 mL; GLYCERIN 1 mL/100 mL; CARBOMER 980 0.35 mL/100 mL; FD&C BLUE NO. 1 0.0001 mL/100 mL; FRAGRANCE CLEAN ORC0600327 0.04 mL/100 mL; ALOE VERA LEAF 0.35 mL/100 mL

Hand Sanitizer

Instant Hand Sanitizer

Warnings
For external use only: hands

Keep out of reach of
children.If swallowed, get
medical help or contact a
Poison Control Center right
away.

Stop use and ask a doctor
if irritation and redness
develop condition persists
for more than 72 hours

aviid contact with broken
skin do not inhale or
ingest

General Warnings

Warnings
For external use only: hands

Keep out of reach of
children.If swallowed, get
medical help or contact a
Poison Control Center right
away.

Stop use and ask a doctor
if irritation and redness
develop condition persists
for more than 72 hours

aviid contact with broken
skin do not inhale or
ingest

ACTIVE INGREDIENT

Ethyl alcohol 70%-75%

INDICATIONS AND USAGE

Use to decrease bacteria on the skin. Use on hands only.

INACTIVE INGREDIENT

Water, Aloe Barbadensis Leaf Juice,
Maltodextrin,Glycerin, Propylene
Glycol, Acrylates/C10-30 Alkyl
Acrylate Crosspolymer,
Triethanoamine, Fragrance, Lactose,
Microcrystalline Cellulose,Sucrose,
Zea Mays(Corn) starch, Ultramarine
blue CI 77007,Tocopheryl Acetate,
Hydroxypropyl Methyl Cellulose,
D&C Red NO.33, FD&C Blue No.1

PURPOSE

To clean hands and fight bacteria on that skin

DOSAGE AND ADMINISTRATION

Squeeze the bottle on your hands so the liquid comes out. Rub hands together. Allow hands to dry.

KEEP OUT OF REACH OF CHILDREN

Not intended for children under the age of 12. Please keep out of reach of children.